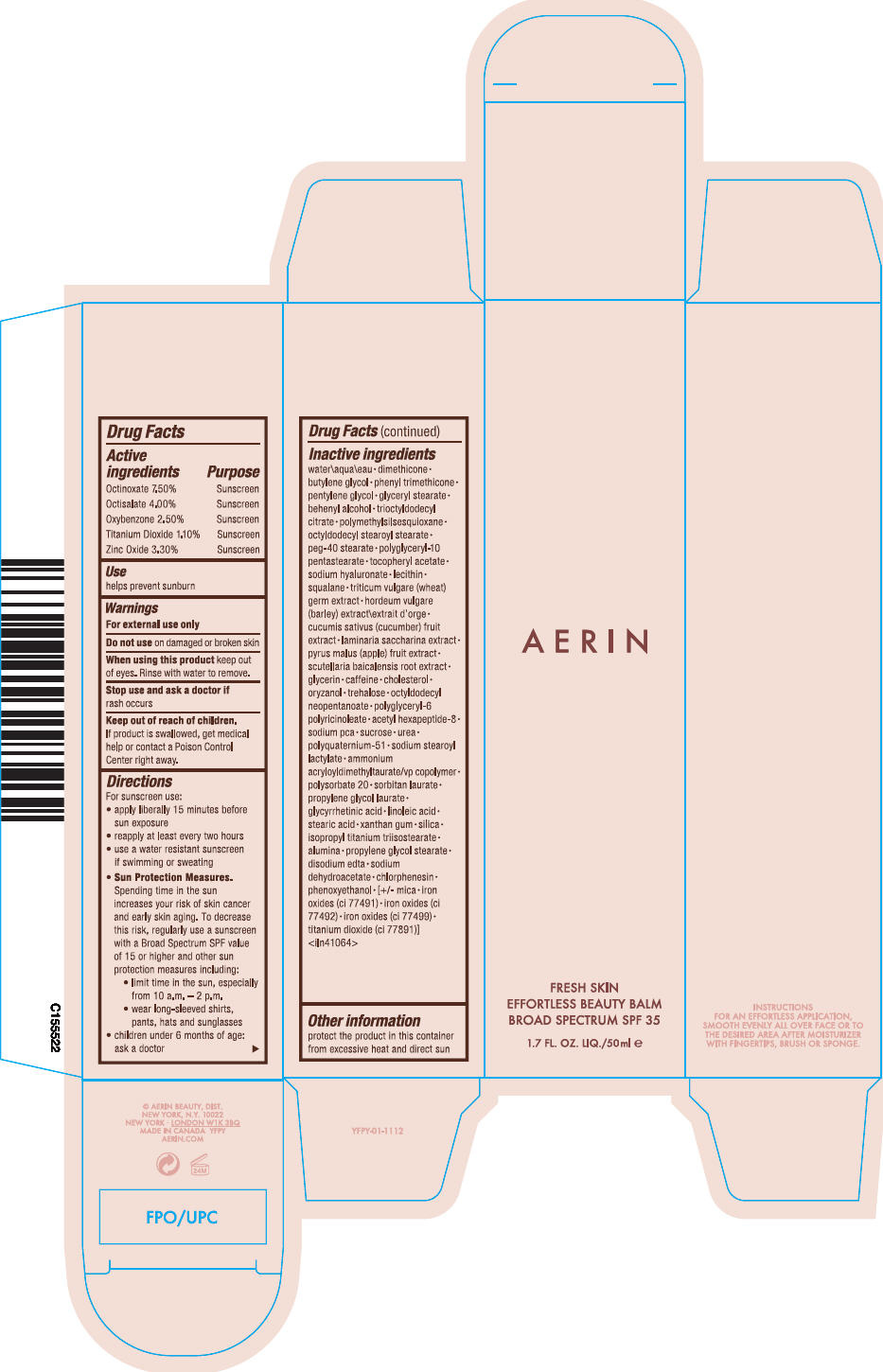 DRUG LABEL: FRESH SKIN EFFORTLESS BEAUTY BALM BROAD SPECTRUM SPF 35
NDC: 43072-001 | Form: CREAM
Manufacturer: AERIN LAUDER BEAUTY DIST.
Category: otc | Type: HUMAN OTC DRUG LABEL
Date: 20141219

ACTIVE INGREDIENTS: OCTINOXATE 0.08175 g/100 mL; OCTISALATE 0.0436 g/100 mL; OXYBENZONE 0.02725 g/100 mL; TITANIUM DIOXIDE 0.01199 g/100 mL; ZINC OXIDE 0.03597 g/100 mL
INACTIVE INGREDIENTS: water; dimethicone; butylene glycol; phenyl trimethicone; pentylene glycol; glyceryl monostearate; docosanol; trioctyldodecyl citrate; octyldodecyl stearoyl stearate; peg-40 stearate; .alpha.-tocopherol acetate; hyaluronate sodium; squalane; wheat germ; barley; cucumber; saccharina latissima; apple; scutellaria baicalensis root; glycerin; caffeine; cholesterol; gamma oryzanol; trehalose; octyldodecyl neopentanoate; acetyl hexapeptide-8; sodium pyrrolidone carboxylate; sucrose; urea; sodium stearoyl lactylate; ammonium acryloyldimethyltaurate/vp copolymer; polysorbate 20; sorbitan monolaurate; propylene glycol monolaurate; enoxolone; linoleic acid; stearic acid; xanthan gum; silicon dioxide; isopropyl titanium triisostearate; aluminum oxide; propylene glycol stearate; edetate disodium; sodium dehydroacetate; chlorphenesin; phenoxyethanol; mica; ferric oxide red; ferric oxide yellow; ferrosoferric oxide

FRESH SKIN EFFORTLESS BEAUTY BALM BROAD SPECTRUM SPF 35

Drug Facts

ACTIVE INGREDIENT

Active ingredients | Purpose
Octinoxate 7.50% | Sunscreen
Octisalate 4.00% | Sunscreen
Oxybenzone 2.50% | Sunscreen
Titanium Dioxide 1.10% | Sunscreen
Zinc Oxide 3.30% | Sunscreen

Use

helps prevent sunburn

Warnings

For external use only

Do not use on damaged or broken skin

When using this product keep out of eyes. Rinse with water to remove.

Stop use and ask a doctor if rash occurs

Keep out of reach of children. If product is swallowed, get medical help or contact a Poison Control Center right away.

Directions

For sunscreen use:

- apply liberally 15 minutes before sun exposure
- reapply at least every two hours
- use a water resistant sunscreen if swimming or sweating
- Sun Protection Measures. Spending time in the sun increases your risk of skin cancer and early skin aging. To decrease this risk, regularly use a sunscreen with a Broad Spectrum SPF value of 15 or higher and other sun protection measures including:
  - limit time in the sun, especially from 10 a.m. – 2 p.m.
  - wear long-sleeved shirts, pants, hats and sunglasses
- children under 6 months of age: ask a doctor

Inactive ingredients

water\aqua\eau • dimethicone • butylene glycol • phenyl trimethicone • pentylene glycol • glyceryl stearate • behenyl alcohol • trioctyldodecyl citrate • polymethylsilsesquioxane • octyldodecyl stearoyl stearate • peg-40 stearate • polyglyceryl-10 pentastearate • tocopheryl acetate • sodium hyaluronate • lecithin • squalane • triticum vulgare (wheat) germ extract • hordeum vulgare (barley) extract\extrait d'orge • cucumis sativus (cucumber) fruit extract • laminaria saccharina extract • pyrus malus (apple) fruit extract • scutellaria baicalensis root extract • glycerin • caffeine • cholesterol • oryzanol • trehalose • octyldodecyl neopentanoate • polyglyceryl-6 polyricinoleate • acetyl hexapeptide-8 • sodium pca • sucrose • urea • polyquaternium-51 • sodium stearoyl lactylate • ammonium acryloyldimethyltaurate/vp copolymer • polysorbate 20 • sorbitan laurate • propylene glycol laurate • glycyrrhetinic acid • linoleic acid • stearic acid • xanthan gum • silica • isopropyl titanium triisostearate • alumina • propylene glycol stearate • disodium edta • sodium dehydroacetate • chlorphenesin • phenoxyethanol • [+/- mica • iron oxides (ci 77491) • iron oxides (ci 77492) • iron oxides (ci 77499) • titanium dioxide (ci 77891)] <iln41064>

Other information

protect the product in this container from excessive heat and direct sun

PRINCIPAL DISPLAY PANEL - 50 ml Tube Carton

AERIN

FRESH SKIN
EFFORTLESS BEAUTY BALM
BROAD SPECTRUM SPF 35

1.7 FL. OZ. LIQ/50ml e